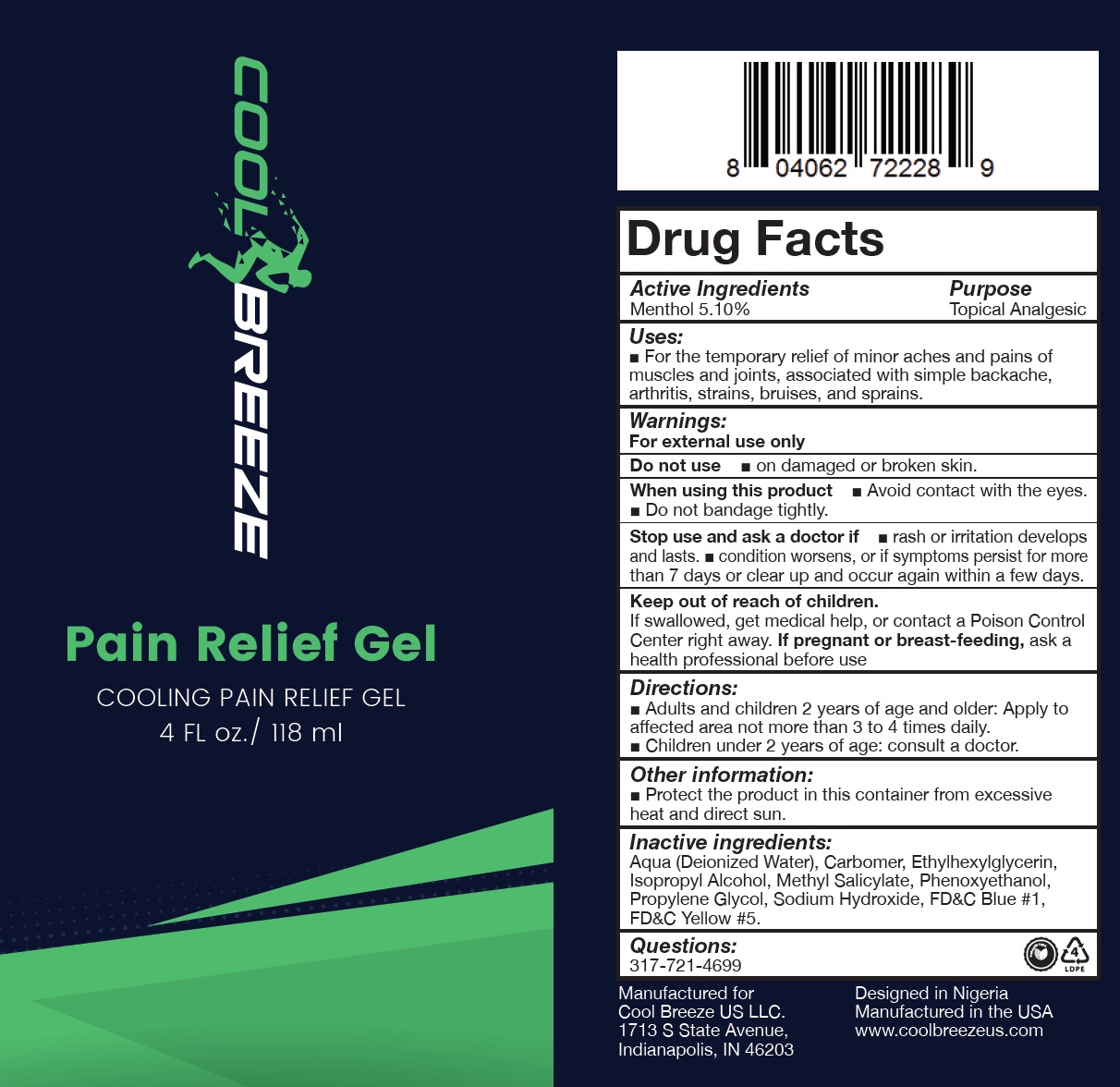 DRUG LABEL: COOL BREEZE Pain Relief
NDC: 72744-433 | Form: GEL
Manufacturer: COOL BREEZE US LLC
Category: otc | Type: HUMAN OTC DRUG LABEL
Date: 20231101

ACTIVE INGREDIENTS: MENTHOL 51 mg/1 mL
INACTIVE INGREDIENTS: WATER; CARBOMER HOMOPOLYMER, UNSPECIFIED TYPE; ETHYLHEXYLGLYCERIN; ISOPROPYL ALCOHOL; METHYL SALICYLATE; PHENOXYETHANOL; PROPYLENE GLYCOL; SODIUM HYDROXIDE; FD&C BLUE NO. 1; FD&C YELLOW NO. 5

COOL BREEZE Pain Relief Gel

Active Ingredients

Menthol 5.10%

Purpose

Topical Analgesic

Uses:

- For the temporary relief of minor aches and pains of muscles and joints, associated with simple backache, arthritis, strains, bruises, and sprains.

Warnings:

For external use only

Do not use

- on damaged or broken skin.

When using this product

- Avoid contact with the eyes.
- Do not bandage tightly.

Stop use and ask a doctor if

- rash or irritation develops and lasts.
- condition worsens, or if symptoms persist for more than 7 days or clear up and occur again within a few days.

Keep out of reach of children.

If swallowed, get medical help, or contact a Poison Control Center right away.

If pregnant or breast-feeding,

ask a health professional before use

Directions:

- Adults and children 2 years of age and older: Apply to affected area not more than 3 to 4 times daily.
- Children under 2 years of age: consult a doctor.

Other information:

- Protect the product in this container from excessive heat and direct sun.

Inactive ingredients:

Aqua (Deionized Water), Carbomer, Ethylhexylglycerin, Isopropyl Alcohol, Methyl Salicylate, Phenoxyethanol, Propylene Glycol, Sodium Hydroxide, FD&C Blue #1, FD&C Yellow #5.

Questions:

317-721-4699